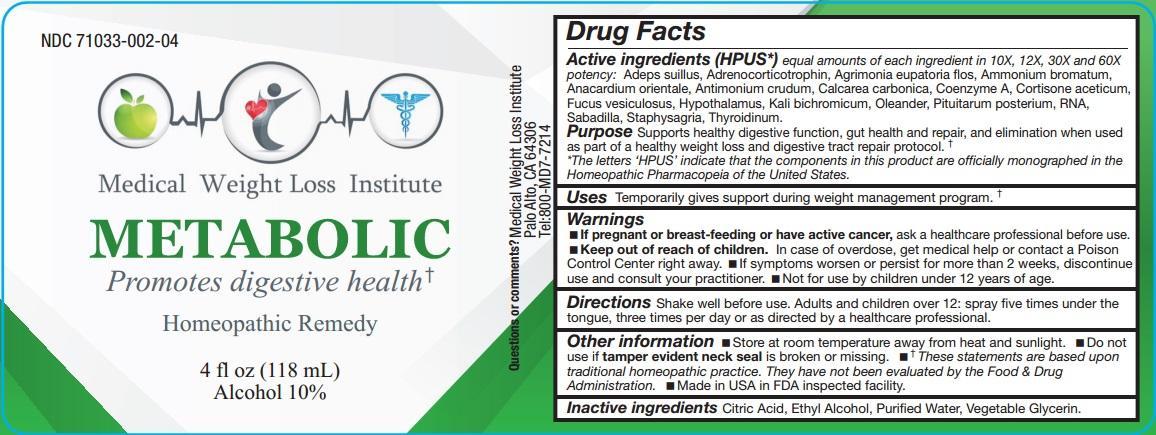 DRUG LABEL: METABOLIC
NDC: 71033-002 | Form: LIQUID
Manufacturer: MEDICAL WEIGHT LOSS INSTITUTE
Category: homeopathic | Type: HUMAN OTC DRUG LABEL
Date: 20161110

ACTIVE INGREDIENTS: LARD 10 [hp_X]/118 mL; CORTICOTROPIN 10 [hp_X]/118 mL; AGRIMONIA EUPATORIA FLOWER 10 [hp_X]/118 mL; AMMONIUM BROMIDE 10 [hp_X]/118 mL; SEMECARPUS ANACARDIUM JUICE 10 [hp_X]/118 mL; ANTIMONY TRISULFIDE 10 [hp_X]/118 mL; OYSTER SHELL CALCIUM CARBONATE, CRUDE 10 [hp_X]/118 mL; COENZYME A 10 [hp_X]/118 mL; CORTISONE ACETATE 10 [hp_X]/118 mL; FUCUS VESICULOSUS 10 [hp_X]/118 mL; BOS TAURUS HYPOTHALAMUS 10 [hp_X]/118 mL; POTASSIUM DICHROMATE 10 [hp_X]/118 mL; NERIUM OLEANDER LEAF 10 [hp_X]/118 mL; SUS SCROFA PITUITARY GLAND 10 [hp_X]/118 mL; SACCHAROMYCES CEREVISIAE RNA 10 [hp_X]/118 mL; SCHOENOCAULON OFFICINALE SEED 10 [hp_X]/118 mL; DELPHINIUM STAPHISAGRIA SEED 10 [hp_X]/118 mL; THYROID, UNSPECIFIED 10 [hp_X]/118 mL
INACTIVE INGREDIENTS: CITRIC ACID MONOHYDRATE; ALCOHOL; WATER; GLYCERIN

METABOLIC

ACTIVE INGREDIENT

Active ingredients (HPUS*) equal amounts of each ingredient in 10X, 12X, 30X and 60X potency:

Adeps suillus, Adrenocorticotrophin, Agrimonia eupatoria flos, Ammonium bromatum, Anacardium orientale, Antimonium crudum, Calcarea carbonica, Coenzyme A, Cortisone aceticum, Fucus vesiculosus, Hypothalamus, Kali bichromicum, Oleander, Pituitarum posterium, RNA, Sabadilla, Staphysagria, Thyroidinum.

Purpose

Supports healthy digestive function, gut health and repair, and elimination when used as part of a healthy weight loss and digestive tract repair protocol.**

*The letters 'HPUS' indicate that the components in this product are officially monographed in the Homeopathic Pharmacopeia of the United States.

Uses

Temporarily gives support during weight management program.**

Warnings

- If pregnant or breast-feeding or have active cancer, ask a healthcare professional before use.
- Keep out of the reach of children. In case of overdose, get medical help or contact a Poison Control Center right away.
- If symptoms worsen or persist for more than 2 weeks, discontinue use and consult your practitioner.
- Not for use by children under 12 years of age.

Keep out of the reach of children.

Directions

Shake well before use. Adults and children over 12: spray five times under the tongue, three times per day or as directed by a healthcare professional.

Other information

- Store at room temperature away from heat and sunlight.
- Do not use if tamper evident neck seal is broken or missing.
- **These statements are based upon traditional homeopathic practice. They have not been evaluated by the Food & Drug Administration.
- Made in USA in FDA inspected facility.

Inactive ingredients

Citric Acid, Ethyl Alcohol, Purified Water, Vegetable Glycerin.

Questions or comments?

Medical Weight Loss Institute

Palo Alto, CA 64306

Tel: 800-MD7-7214

PURPOSE

Promotes digestive health**

PACKAGE LABEL

NDC 71033-002-04

Medical Weight Loss Institute

METABOLIC

Promotes digestive health**

Homeopathic Remedy

4 fl oz (118 mL)

Alcohol 10%